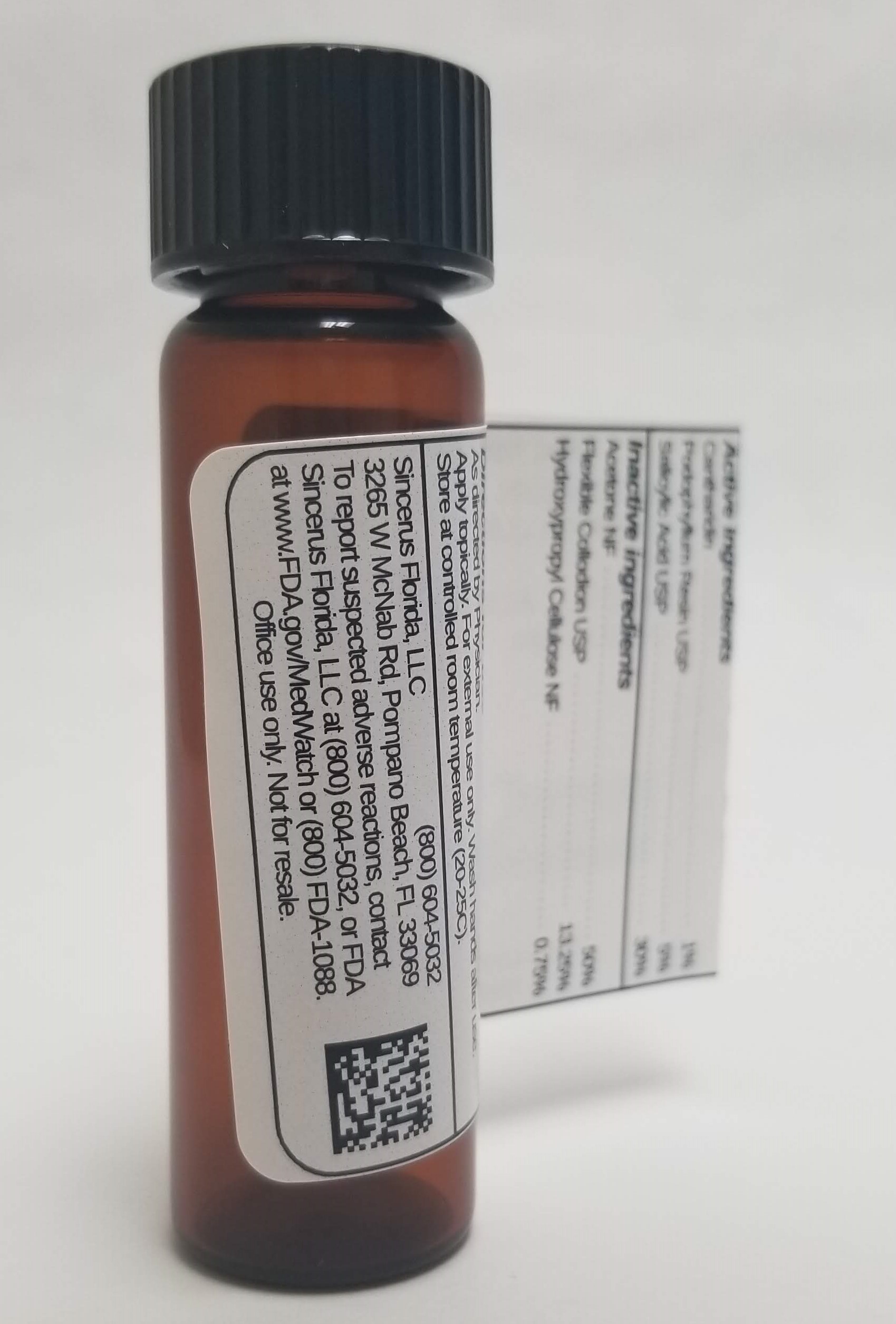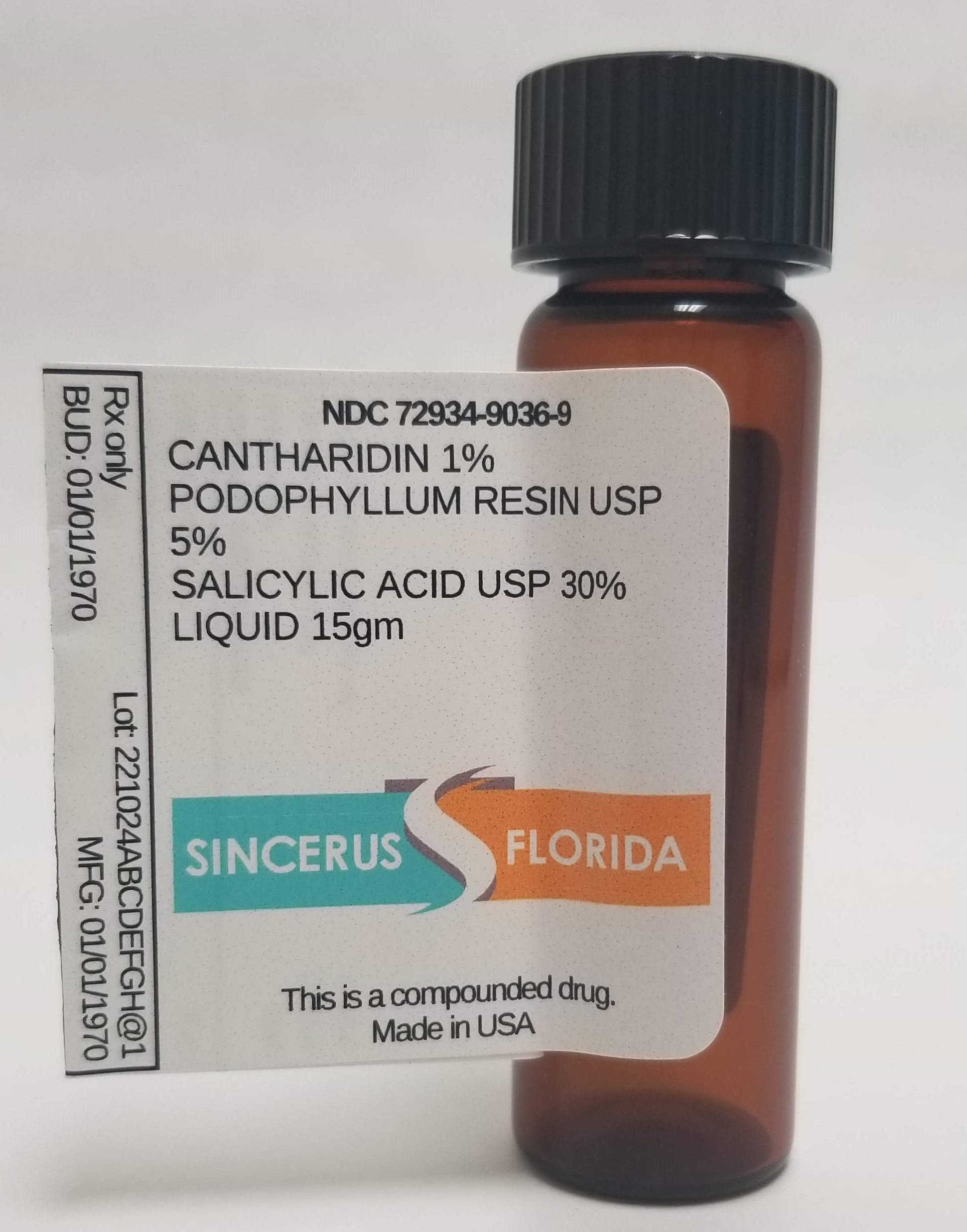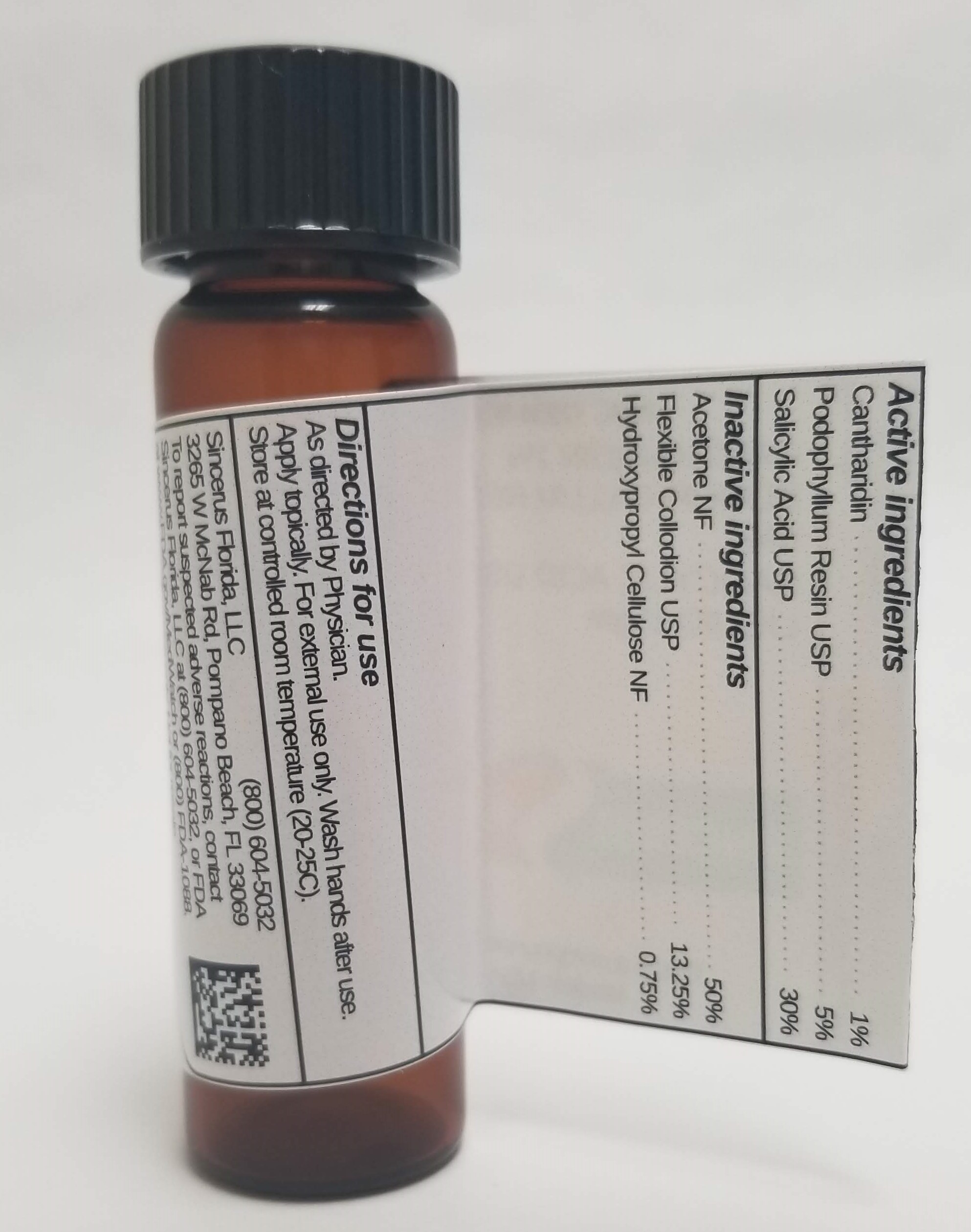 DRUG LABEL: CANTHARIDIN 1% / PODOPHYLLUM RESIN 5% / SALICYLIC ACID 30%
NDC: 72934-9036 | Form: LIQUID
Manufacturer: Sincerus Florida, LLC
Category: prescription | Type: HUMAN PRESCRIPTION DRUG LABEL
Date: 20190517

ACTIVE INGREDIENTS: SALICYLIC ACID 30 g/100 g; CANTHARIDIN 1 g/100 g; PODOPHYLLUM RESIN 5 g/100 g

CANTHARIDIN 1% / PODOPHYLLUM RESIN 5% / SALICYLIC ACID 30%